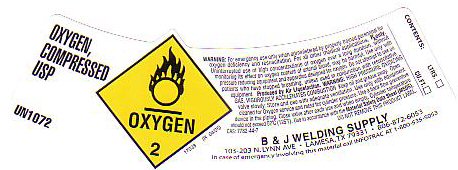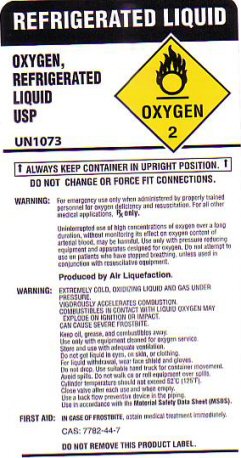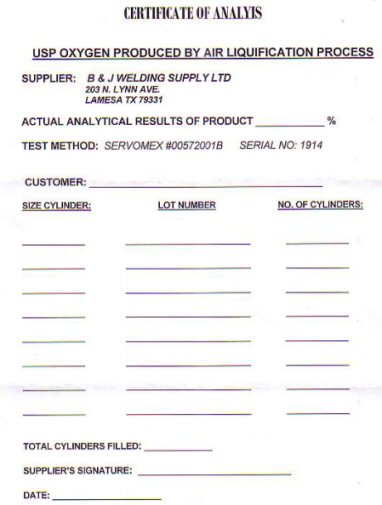 DRUG LABEL: OXYGEN
NDC: 67573-0101 | Form: GAS
Manufacturer: B&J Welding Supply LTD
Category: prescription | Type: HUMAN PRESCRIPTION DRUG LABEL
Date: 20120703

ACTIVE INGREDIENTS: OXYGEN 99.5 L/100 L

OXYGEN COMPRESSED LABEL

OXYGEN COMPRESSED USP UN 1072 OXYGEN-2 PRODUCED BY AIR LIQUEFACTION. CAS 7782-44-7 17033 (R 04/05)

CONTENTS _____________ LITERS ______________ CU FT

IN CASE OF EMERGENCY INVOLVING THIS MATERIAL CALL INFOTRAC AT 1-800-535-5053

OXYGEN REFRIGERATED LIQUID LABEL

REFRIGERATED LIQUID OXYGEN REFRIGERATED LIQUID USP UN 1073 OXYGEN-2

ALWAYS KEEP CONTAINER IN UPRIGHT POSITION DO NOT CHANGE OR FORCE FIT CONNECTIONS

WARNING: EXTREMELY COLD OXIDIZING LIQUID AND GAS UNDER PRESSURE COMBUSTIBLES IN CONTACT WITH LIQUID OXYGEN MAY EXPLODE ON IGNITION OR IMPACT. CAN CAUSE SEVERE FROSTBITE. DO NOT GET LIQUID IN EYES ON SKIN OR CLOTHING. FOR LIQUID WITHDRAWAL WEAR FACE SHIELD AND GLOVES. DO NOT DROP. USE SUITABLE HAND TRUCK FOR CONTAINER MOVEMENT. AVOID SPILLS.

IN CASE OF FROSTBITE OBTAIN MEDICAL TREATMENT IMMEDIATELY. CAS 7782-44-7 41533 (R 10/04) IN CASE OF EMERGENCY INVOLVING THIS MATERIAL CALL INFOTRAC AT 1-800-535-5053

OXYGEN CERTIFICATE OF ANALYSIS

CERTIFICATE OF ANALYSIS USP OXYGEN PRODUCED BY AIR LIQUEFACTION PROCESS SUPPLIER B AND J WELDING SUPPLY LTD 203 N LYNN AVE LAMESA TX 79331

ACTUAL ANALYTICAL RESULTS OF PRODUCT _________% TEST METHOD: SERVOMEX #00572001B SERIAL NO 1914

CUSTOMER______________ SIZE CYLINDER_____ LOT NUMBER_________ NO OF CYLINDERS_____________ TOTAL CYLINDERS SUPPLIED___________ SUPPLIERS SIGNATURE_______________ DATE_____________

PRODUCT WARNINGS AND PRECAUTIONS

FOR EMERGENCY USE ONLY WHEN ADMINISTERED BY PROPERLY TRAINED PERSONNEL FOR OXYGEN DEFICIENCY AND RESUSCITATION. FOR ALL OTHER MEDICAL APPLICATIONS Rx ONLY. UNINTERRUPTED USE OF HIGH CONCENTRATIONS OF OXYGEN OVER A LONG DURATION WITHOUT MONITORING ITS EFFECT ON OXYGEN CONTENT OF ARTERIAL BLOOD MAY BE HARMFUL. USE ONLY WITH PRESSURE REDUCING EQUIPMENT AND APPARATUS DESIGNED FOR OXYGEN. DO NOT ATTEMPT TO USE ON PATIENTS WHO HAVE STOPPED BREATHING UNLESS USED IN CONJUNCTION WITH RESUSCITATIVE EQUIPMENT.

VIGOROUSLY ACCELERATES COMBUSTION. KEEP OIL AND GREASE AWAY. USE ONLY WITH EQUIPMENT CLEANED FOR OXYGEN SERVICE AND RATED FOR CYLINDER PRESSURE. USE A BACK FLOW PREVENTATIVE DEVICE IN THE PIPING. CLOSE VALVE AFTER EACH USE AND WHEN EMPTY. CYLINDER TEMPERATURE SHOULD NOT EXCEED 52 C (125 F). USE IN ACCORDANCE WITH THE MATERIAL SAFETY DATA SHEET (MSDS). DO NOT REMOVE THIS PRODUCT LABEL.